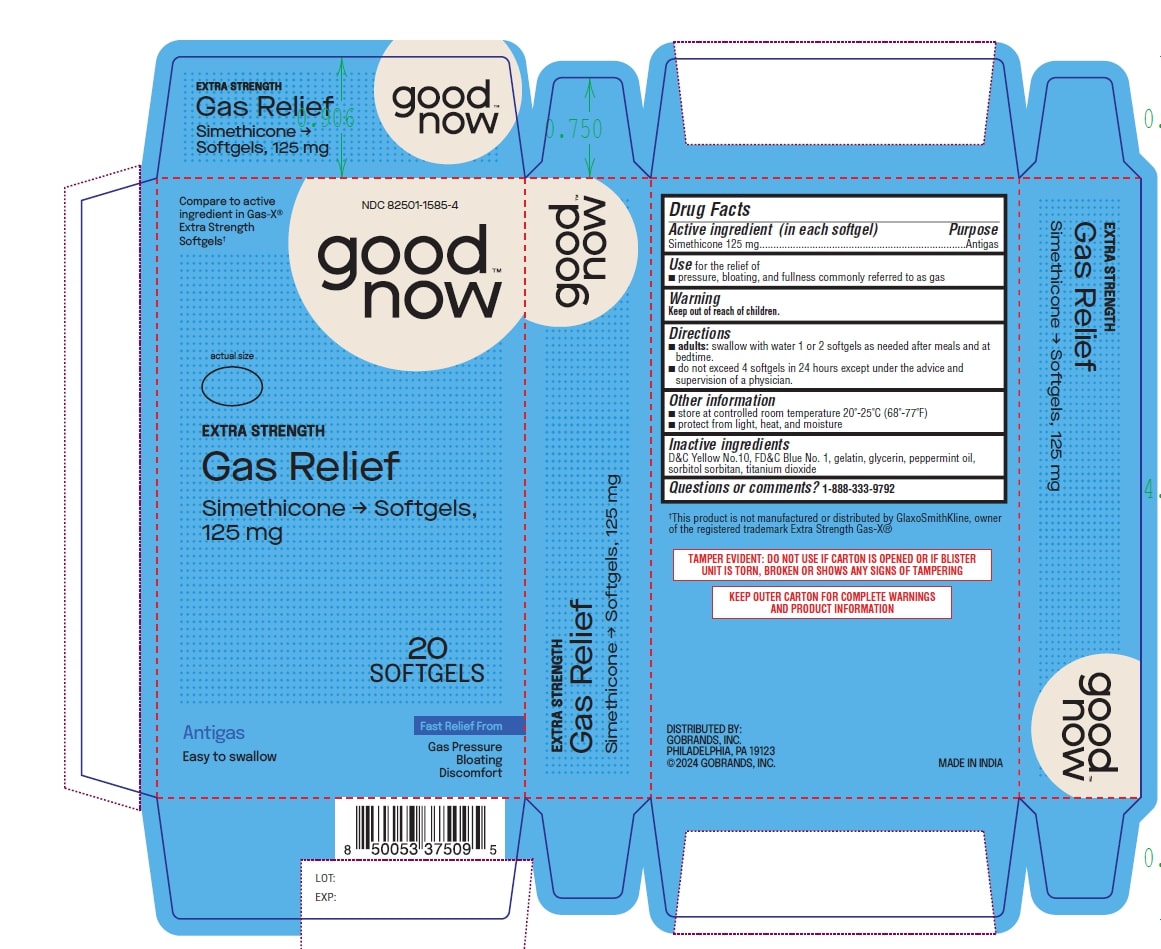 DRUG LABEL: Good Now Extra Strength Gas Relief
NDC: 82501-1588 | Form: CAPSULE, LIQUID FILLED
Manufacturer: Gobrands, Inc
Category: otc | Type: HUMAN OTC DRUG LABEL
Date: 20241220

ACTIVE INGREDIENTS: DIMETHICONE 125 mg/1 1
INACTIVE INGREDIENTS: D&C YELLOW NO. 10; FD&C BLUE NO. 1; GELATIN; GLYCERIN; PEPPERMINT OIL; SORBITOL SOLUTION; TITANIUM DIOXIDE

Good Now Extra Strength Gas Relief